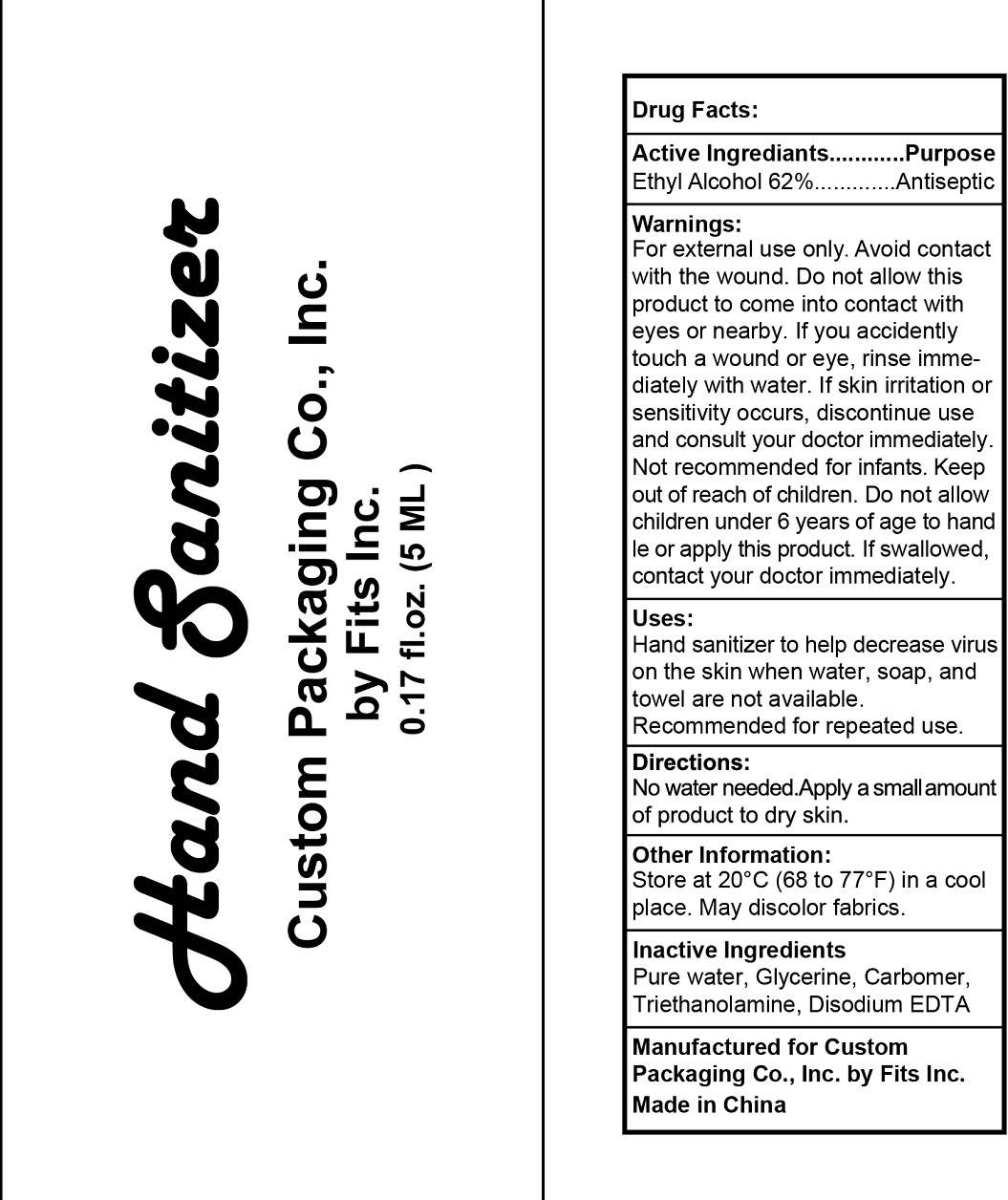 DRUG LABEL: Hand Sanitizer
NDC: 82447-103 | Form: LIQUID
Manufacturer: Meizhou Jubona Technology Co., Ltd.
Category: otc | Type: HUMAN OTC DRUG LABEL
Date: 20211213

ACTIVE INGREDIENTS: ALCOHOL 62 mL/100 mL
INACTIVE INGREDIENTS: GLYCERIN; WATER; TROLAMINE; EDETATE DISODIUM

Drug Fact

Active Ingredient

Ethyl Alcohol 62%

Purpose

Antiseptic

Uses

- Hand sanitizer to helo decrease virus on the skin when water,soap and towel are not available.
- recommended for repeared use.

Warnings

For external use only. Avoid contact with the wound. Do not allow this product to come into contact with eyes or nearby.

If you accidently touch a wound or eye, rinse immediately with water.

If skin irritation or sensitivity occurs ,discontinue use and consult your doctor immediately.

Not recommended for infants.

Other information:

Store at 20℃（68 to 77 ℉）in a cool place . May discolor fabrics.

Keep out of reach of children.

Do not allow children under 6 years of age to handle or apply this product，If swallowed ,contact your doctor immediately.

Directions

No water needed . Apply a small amount of product to dry skin.

Inactive Ingredients

Pure Water, Glycerine, Carbomer, Triethanolamine, Disodium EDTA